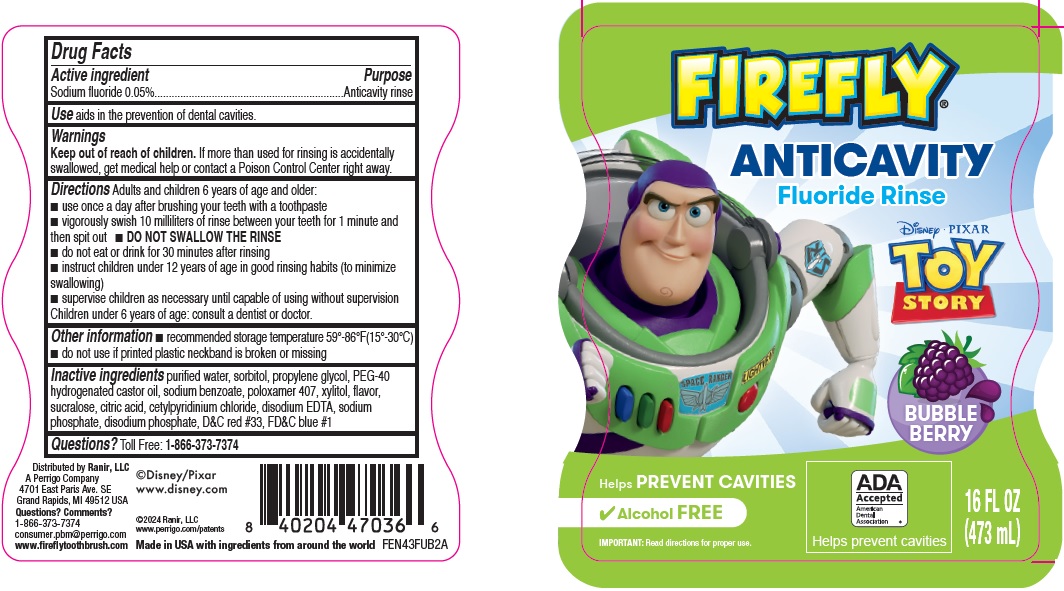 DRUG LABEL: Firefly Anticavity Fluoride
NDC: 66923-111 | Form: RINSE
Manufacturer: Ranir LLC
Category: otc | Type: HUMAN OTC DRUG LABEL
Date: 20241120

ACTIVE INGREDIENTS: SODIUM FLUORIDE .5 mg/1 mL
INACTIVE INGREDIENTS: WATER; SORBITOL; PROPYLENE GLYCOL; POLYOXYL 40 HYDROGENATED CASTOR OIL; SODIUM BENZOATE; POLOXAMER 407; XYLITOL; SUCRALOSE; CITRIC ACID MONOHYDRATE; CETYLPYRIDINIUM CHLORIDE; EDETATE DISODIUM ANHYDROUS; SODIUM PHOSPHATE; SODIUM PHOSPHATE, DIBASIC, ANHYDROUS; D&C RED NO. 33; FD&C BLUE NO. 1

FIREFLY Anticavity Fluoride Rinse Toy Story Drug Facts

Active ingredient

Sodium fluoride 0.05%

Purpose

Anticavity rinse

Use

aids in the prevention of dental cavities.

Warnings

Keep out of reach of children.

If more than used for rinsing is accidentally swallowed, get medical help or contact a Poison Control Center right away.

Directions

Adults and children 6 years of age and older:

- use once a day after brushing your teeth with a toothpaste
- vigorously swish 10 milliliters of rinse between your teeth for 1 minute and then spit out
- DO NOT SWALLOW THE RINSE
- do not eat or drink for 30 minutes after rinsing
- instruct children under 12 years of age in good rinsing habits (to minimize swallowing)
- supervise children as necessary until capable of using without supervision
  Children under 6 years of age: consult a dentist or doctor.

Other information

- recommended storage temperature 59°-86°F(15°-30°C)
- do not use if printed plastic neckband is broken or missing

Inactive Ingredients

purified water, sorbitol, propylene glycol, PEG-40 hydrogenated castor oil, sodium benzoate, poloxamer 407, xylitol, flavor, sucralose, citric acid, cetylpyridinium chloride, disodium EDTA, sodium phosphate, disodium phosphate, D&C red #33, FD&C blue #1

Questions?

Toll Free: 1-866-373-7374

Principal Display Panel

FIREFLY® ANTICAVITY Fluoride Rinse

Disney PIXAR

TOY STORY

BUBBLE BERRY

Helps PREVENT CAVITIES

ADA Accepted American Dental Association®

Helps prevent cavities

Alcohol FREE

IMPORTANT: Read directions for proper use.

16 FL OZ (473 mL)